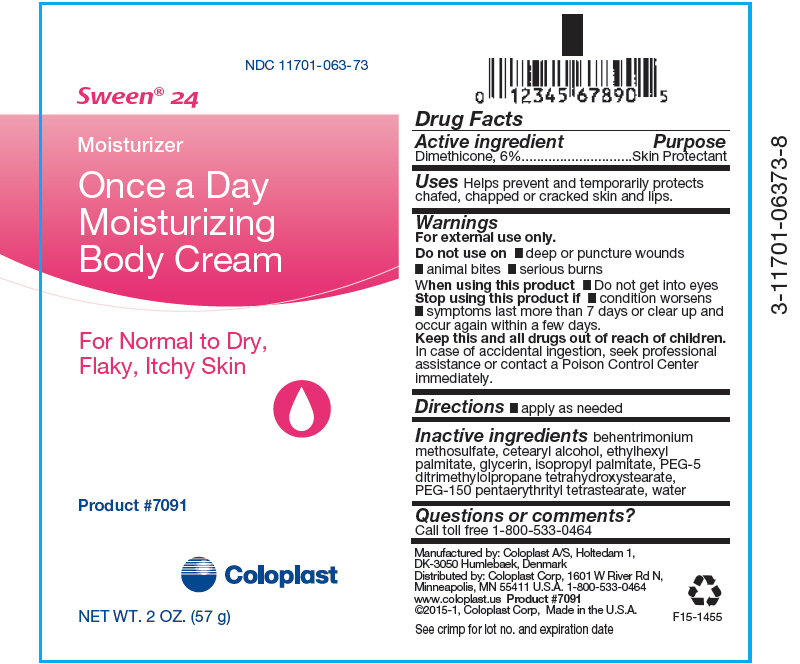 DRUG LABEL: Sween 24
NDC: 11701-063 | Form: CREAM
Manufacturer: Coloplast Manufacturing US, LLC
Category: otc | Type: HUMAN OTC DRUG LABEL
Date: 20231221

ACTIVE INGREDIENTS: DIMETHICONE 60 mg/1 g
INACTIVE INGREDIENTS: BEHENTRIMONIUM METHOSULFATE; CETOSTEARYL ALCOHOL; ETHYLHEXYL PALMITATE; GLYCERIN; ISOPROPYL PALMITATE; PEG-150 PENTAERYTHRITYL TETRASTEARATE; WATER

Sween® 24

Drug Facts

Active ingredient

Dimethicone, 6%

Purpose

Skin Protectant

Uses

Helps prevent and temporarily protects chafed, chapped or cracked skin and lips.

Warnings

For external use only.

Do not use on

- deep or puncture wounds
- animal bites
- serious burns

When using this product

- Do not get into eyes

Stop using this product if

- condition worsens
- symptoms last more than 7 days or clear up and occur again within a few days.

KEEP OUT OF REACH OF CHILDREN

Keep this and all drugs out of reach of children.

In case of accidental ingestion, seek professional assistance or contact a Poison Control Center immediately.

Directions

- apply as needed

Inactive ingredients

behentrimonium methosulfate, cetearyl alcohol, ethylhexyl palmitate, glycerin, isopropyl palmitate, PEG-5 ditrimethylolpropane tetrahydroxystearate, PEG-150 pentaerythrityl tetrastearate, water

Questions or comments?

Call toll free 1-800-533-0464

Manufactured by: Coloplast A/S, Holtedam 1,
DK-3050 Humlebaek, Denmark
Distributed by: Coloplast Corp, 1601 W River Rd N,
Minneapolis, MN 55411 U.S.A.

PRINCIPAL DISPLAY PANEL - 57 g Tube Label

NDC 11701-063-73

Sween® 24

Moisturizer
Once a Day
Moisturizing
Body Cream

For Normal to Dry,
Flaky, Itchy Skin

Product #7091

Coloplast

NET WT. 2 OZ. (57 g)